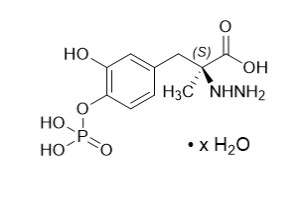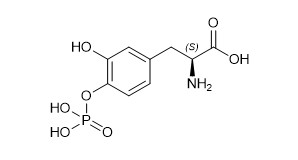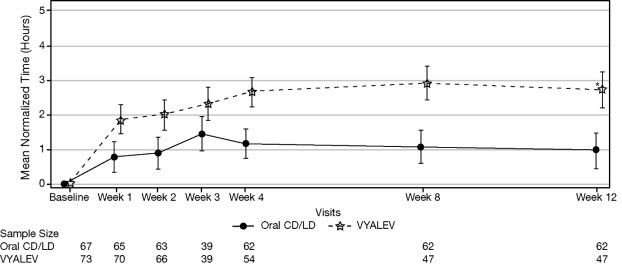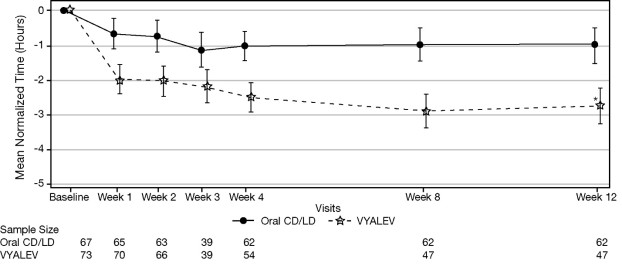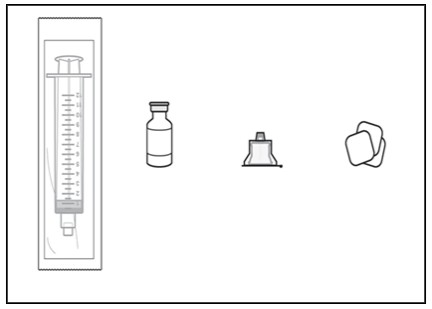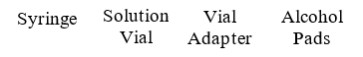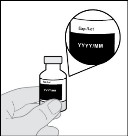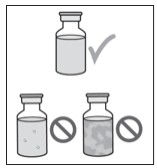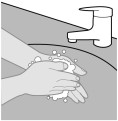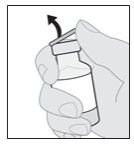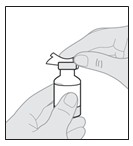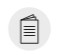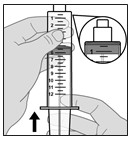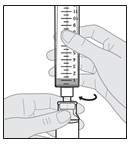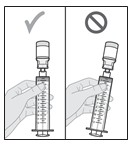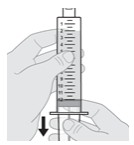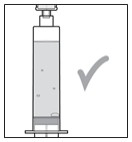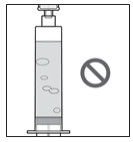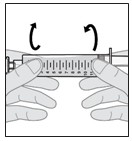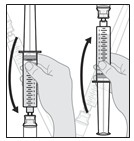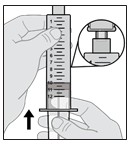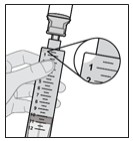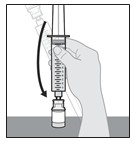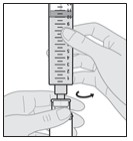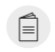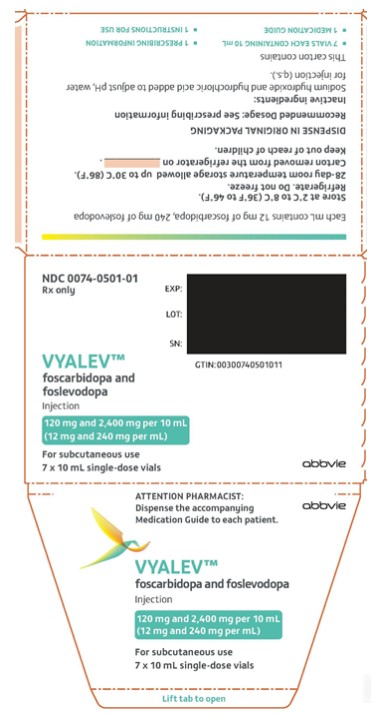 DRUG LABEL: Vyalev
NDC: 0074-0501 | Form: INJECTION
Manufacturer: AbbVie Inc.
Category: prescription | Type: HUMAN PRESCRIPTION DRUG LABEL
Date: 20241016

ACTIVE INGREDIENTS: FOSCARBIDOPA 12 mg/1 mL; FOSLEVODOPA 240 mg/1 mL
INACTIVE INGREDIENTS: WATER; SODIUM HYDROXIDE; HYDROCHLORIC ACID

HIGHLIGHTS OF PRESCRIBING INFORMATION

These highlights do not include all the information needed to use VYALEV safely and effectively. See full prescribing information for VYALEV.
VYALEV™ (foscarbidopa and foslevodopa) injection, for subcutaneous use
Initial U.S. Approval: 1975

1 INDICATIONS AND USAGE

VYALEV is a combination of foscarbidopa (an aromatic amino acid decarboxylation inhibitor) and foslevodopa (an aromatic amino acid) indicated for the treatment of motor fluctuations in adults with advanced Parkinson’s disease. (1)

2 DOSAGE AND ADMINISTRATION

- For subcutaneous administration only, preferably in the abdomen, via the VYAFUSER pump. (2.1, 2.2, 2.3)
- See the Full Prescribing Information for calculation of the base continuous dosage, hourly infusion rate, optional loading dose, and extra dose. (2.2)
- The maximum recommended daily dosage of VYALEV is 3,525 mg of foslevodopa (approximately 2,500 mg levodopa). (2.2)

3 DOSAGE FORMS AND STRENGTHS

Injection: 120 mg foscarbidopa and 2,400 mg foslevodopa per 10 mL (12 mg foscarbidopa and 240 mg foslevodopa per mL). (3)

4 CONTRAINDICATIONS

VYALEV is contraindicated in patients who are currently taking a nonselective monoamine oxidase (MAO) inhibitor or have recently (within 2 weeks) taken a nonselective MAO inhibitor. (4)

5 WARNINGS AND PRECAUTIONS

- May cause falling asleep during activities of daily living. (5.1)
- Hallucinations/Psychosis: May respond to dose reduction of VYALEV. (5.2)
- Impulse Control Behaviors: Consider dose reductions or stopping VYALEV. (5.3)
- Infusion Site Reactions and Infections: Monitor for infusion site infections: Following aseptic techniques while using this medication and frequent rotation of the infusion site is recommended to reduce the risk. (5.4)
- Avoid sudden discontinuation or rapid dose reduction to reduce the risk of withdrawal-emergent hyperpyrexia and confusion. (5.5)
- May cause or exacerbate dyskinesia: Consider dose reduction of VYALEV. (5.6)

6 ADVERSE REACTIONS

Most common adverse reactions for VYALEV (VYALEV incidence at least 10% and greater than oral carbidopa-levodopa incidence) were infusion/catheter site reactions, infusion/catheter site infections, hallucinations, and dyskinesia. (6.1)

To report SUSPECTED ADVERSE REACTIONS, contact AbbVie Inc. at 1-800-633-9110 or FDA at 1-800-FDA-1088 or www.fda.gov/medwatch.

7 DRUG INTERACTIONS

- Selective MAO-B inhibitors: May cause orthostatic hypotension. (7.1)
- Antihypertensive drugs: May cause symptomatic postural hypotension. Dosage adjustment of the antihypertensive drug may be needed. (7.2)
- Dopamine D2 receptor antagonists and isoniazid may reduce the effectiveness of VYALEV. (7.3)

8 USE IN SPECIFIC POPULATIONS

Pregnancy: Based on animal data, may cause fetal harm. (8.1)

FULL PRESCRIBING INFORMATION

1 INDICATIONS AND USAGE

VYALEV is indicated for the treatment of motor fluctuations in adults with advanced Parkinson’s disease (PD).

2 DOSAGE AND ADMINISTRATION

2.1 Important Information

For subcutaneous administration only.

Patients selected for treatment with VYALEV should be capable of understanding and using the delivery system [see Healthcare Professional Instructions for Use of VYAFUSER Pump, and Patient Instructions for Use of VYAFUSER Pump] themselves or with assistance from a caregiver.

Patients should be trained on the proper use of VYALEV and the delivery system prior to initiating.

2.2 Recommended Dosage

VYALEV (foscarbidopa and foslevodopa) is administered as a subcutaneous infusion with the VYAFUSER pump [see Dosage and Administration (2.3), Healthcare Professional Instructions for Use of VYAFUSER Pump, and Patient Instructions for Use of VYAFUSER Pump].

VYALEV Base Continuous Dosage and Hourly Infusion Rate

The continuous infusion rate is based on total levodopa dosage (TLD). The hourly base continuous infusion rate (mL/hr) = [(TLD x 1.3) / 240] / [number of hours the patient is typically awake (e.g., 16 hours)], as shown in the steps below.

Step 1: Calculate the TLD for the levodopa-containing medications that VYALEV is replacing. All dosages should be converted to the equivalent dosage of immediate-release levodopa to obtain the TLD. Prescribers should adjust the total dose of levodopa-containing products for COMT inhibitor use. See the Prescribing Information for the respective drugs for conversions or adjustments. Do not include rescue or as needed levodopa or any other anti-Parkinsonian medication or therapy, including medications taken outside of awake time (e.g., night-time dosing) in this calculation.

Step 2: Determine the total daily dosage (mg) of VYALEV foslevodopa component by multiplying the TLD by 1.3. The conversion factor takes into account the molecular weight and bioavailability of foslevodopa compared to levodopa.

Step 3: Determine the total daily volume (mL) of VYALEV by dividing the total daily dosage (mg) of VYALEV by 240. Each 1 mL of VYALEV contains 240 mg of foslevodopa.

Step 4: Determine the hourly base continuous infusion rate of VYALEV by dividing the total daily volume (mL) of VYALEV by the number of hours the patient is typically awake (e.g., 16 hours). VYALEV may be administered over the patient’s waking hours or may be administered for 24 hours. See Dosage and Administration (2.3) for adjustment of and alternate infusion rates for lower overnight dosages.

Maximum Dosage

The maximum recommended daily dosage of VYALEV is 3,525 mg of the foslevodopa component (equivalent to approximately 2,500 mg levodopa).

Optional Loading Dose

If VYALEV therapy is being initiated in an “Off” state or the patient has not been receiving their base continuous infusion for more than 3 hours, a loading dose can be administered immediately prior to starting or re-starting the base continuous hourly infusion. Loading doses can be administered either with VYALEV or patients can continue using oral immediate-release carbidopa/levodopa tablets. The loading dose should be calculated from the first morning dose of oral immediate release carbidopa/levodopa the patient took before starting treatment with VYALEV. If VYALEV is used for the loading dose, multiply the first morning dose of oral immediate release levodopa by 1.3 and divide by 240 to determine the loading dose of VYALEV.

The pump is capable of delivering a loading dose ranging from 0.1 mL to a maximum of 3 mL, in increments of 0.1 mL.

Extra Dose

An extra dose volume can be programmed to 1 of 5 options (see Table 1). The “extra dose” feature is limited to no more than 1 extra dose per hour. If 2 or more extra doses are used by the patient during the 24-hour/day treatment period, a revision of the base continuous infusion rate should be considered (refer to the Healthcare Professional Instructions for Use of VYAFUSER Pump details).

Table 1. Extra Dose Option for VYALEV
VYALEV extra dose volume | Approximate equivalent levodopa dose*
0.1 mL | 17 mg
0.15 mL | 25.5 mg
0.2 mL | 34 mg
0.25 mL | 42.5 mg
0.3 mL | 51 mg

*See Step 1

2.3 Preparation and Administration Instructions

Patients should be trained on the proper use of VYALEV and the delivery system prior to initiating treatment with VYALEV and, as necessary, thereafter [see Dosage and Administration (2.2) and the Patient Instructions for Use of VYAFUSER Pump].

Preparation

- Use aseptic technique.
- Use sterile, single-patient-use infusion components (syringe, infusion set, and vial adapter) qualified for use with the pump to infuse VYALEV.
- Do not dilute.
- Do not mix VYALEV with other products.
- The medication vials are for single dose only. The entire contents of a VYALEV vial should be transferred into a syringe for administration. Do not withdraw a partial portion of the vial contents.
- Parenteral drug products should be inspected visually for particulate matter and discoloration prior to administration, whenever solution and container permit [see Dosage Forms and Strengths (3)].
- The infusion set (cannula) can remain in place for up to 3 days when VYALEV is infused continuously.

Administration

Site Selection

- Administer VYALEV subcutaneously, preferably in the abdomen, avoiding the area with a 2-inch radius from the navel.
- Rotate the infusion site and use a new infusion set at least every 3 days.
- Select new infusion sites at least 1 inch from sites used within the previous 12 days.
- Do not infuse VYALEV into areas where the site is tender, bruised, red, or hard to the touch.

Infusion Flow Rates

- Adjustment: Infusion rates may be adjusted in increments of 0.01 mL/hr (which is equivalent to approximately 1.7 mg of levodopa/hour).
- Alternative Flow Rates: The healthcare professional has the option to enable and pre-program the pump with 2 alternative continuous infusion rates (Low/High) that the patient may select to account for changes in functional demand (e.g., lowering the dosage at night or increasing the dose for prolonged intense activity) (see the Healthcare Professional Instructions for Use of VYAFUSER Pump).

Discarding VYALEV and Syringe

- Discard the vial after transfer of the product to the syringe. Discard the syringe and any unused VYALEV in the syringe after the product has been in the syringe for 24 hours.

2.4 Interruption of Therapy

Prescribing a backup oral carbidopa and levodopa product is recommended in the event that delivery of VYALEV is interrupted, which may result in underdosing. Sudden discontinuation or rapid dose reduction of VYALEV, without administration of alternative dopaminergic therapy, should be generally avoided [see Warnings and Precautions (5.5)].

Following interruptions of more than 1 hour, a new infusion set (tubing and cannula) should be used and rotated to a different infusion site. If the infusion has been interrupted for longer than 3 hours, the patient may also self-administer a loading dose, if enabled by their healthcare professional [see Dosage and Administration (2.2)].

3 DOSAGE FORMS AND STRENGTHS

Injection: 120 mg foscarbidopa and 2,400 mg foslevodopa per 10 mL (12 mg foscarbidopa and 240 mg foslevodopa per mL). Each single-dose vial contains 10 mL of a colorless to yellow to brown (may have a purple or red tint) and clear to slightly opalescent solution.

4 CONTRAINDICATIONS

VYALEV is contraindicated in patients who are currently taking a non-selective monoamine oxidase (MAO) inhibitor or have recently (within 2 weeks) taken a nonselective MAO inhibitor. Hypertension can occur if these drugs are used concurrently [see Drug Interactions (7.1)].

5 WARNINGS AND PRECAUTIONS

5.1 Falling Asleep During Activities of Daily Living and Somnolence

Patients treated with levodopa (the active metabolite of VYALEV) have reported falling asleep while engaged in activities of daily living, including the operation of motor vehicles, which sometimes resulted in accidents. Although many of these patients reported somnolence while on levodopa, some perceived that they had no warning signs, such as excessive drowsiness, and believed that they were alert immediately prior to the event (sleep attack). Some of these events have been reported more than one year after initiation of treatment.

Falling asleep while engaged in activities of daily living usually occurs in patients experiencing preexisting somnolence, although patients may not give such a history. For this reason, prescribers should reassess patients for drowsiness or sleepiness while using VYALEV, especially since some of the events occur well after the start of treatment. Prescribers should be aware that patients may not acknowledge drowsiness or sleepiness until directly questioned about drowsiness or sleepiness during specific activities. Patients who have already experienced somnolence or an episode of sudden sleep onset should not participate in these activities while taking VYALEV.

Before initiating treatment with VYALEV, advise patients about the potential to develop drowsiness and specifically ask about factors that may increase the risk for somnolence with VYALEV such as the use of concomitant sedating medications or the presence of sleep disorders. Consider discontinuing VYALEV in patients who report significant daytime sleepiness or episodes of falling asleep during activities that require active participation (e.g., conversations, eating). If VYALEV is continued, patients should be advised not to drive and to avoid other potentially dangerous activities that might result in harm if the patient becomes somnolent. There is insufficient information to establish that dose reduction will eliminate episodes of falling asleep while engaged in activities of daily living.

5.2 Hallucinations/Psychosis

There is an increased risk for hallucinations and psychosis in patients taking VYALEV. In Study 1 [see Clinical Studies (14)], hallucinations occurred in 12.2% of patients treated with VYALEV compared to 1.5% of patients treated with oral immediate-release carbidopa-levodopa. Psychosis occurred in 4.1% of patients treated with VYALEV compared to 1.5% of patients treated with oral immediate-release carbidopa-levodopa. Treatment with VYALEV was discontinued in 1 (1.4%) patient because of hallucinations.

Hallucinations associated with levodopa may present shortly after the initiation of therapy and may be responsive to dose reduction of VYALEV or other concomitantly administered medications. Confusion, insomnia, and excessive dreaming may accompany hallucinations. Abnormal thinking and behavior may present with one or more symptoms, including paranoid ideation, delusions, hallucinations, confusion, psychosis, disorientation, aggressive behavior, agitation, and delirium. Review of treatment is recommended if these symptoms develop.

Because of the risk of exacerbating psychosis, patients with a major psychotic disorder should not be treated with VYALEV. In addition, medications that antagonize the effects of dopamine used to treat psychosis may exacerbate the symptoms of PD and may decrease the effectiveness of VYALEV [see Drug Interactions (7.3)].

5.3 Impulse Control/Compulsive Behaviors

Patients may experience intense urges to gamble, increased sexual urges, intense urges to spend money, binge or compulsive eating, and/or other intense urges, and the inability to control these urges while taking one or more of the medications, including VYALEV, that increase central dopaminergic tone and that are generally used for the treatment of PD. In some cases, although not all, these urges were reported to have stopped when the dose was reduced, or the medication was discontinued.

Because patients may not recognize these behaviors as abnormal, it is important for prescribers to ask patients or their caregivers specifically about the development of new or increased gambling urges, sexual urges, uncontrolled spending, binge or compulsive eating, or other urges while being treated with VYALEV. Consider reducing the dose or discontinuing VYALEV if a patient develops such urges.

5.4 Infusion Site Reactions and Infections

VYALEV can cause infusion site reactions and infections.

In Study 1, one or more infusion site reactions were reported in 62% of patients treated with VYALEV and 8% of patients who received placebo subcutaneous infusion. Various types of reactions at the infusion site have been reported including: erythema, pain, edema, nodule, bruising, hemorrhage, induration, pruritus, extravasation, inflammation, mass, warmth, hematoma, pallor, rash, and swelling. In Study 1, 8% of patients treated with VYALEV and no patient who received placebo withdrew from treatment because of an infusion site reaction.

In Study 1, infusion site infections occurred in 28% of patients treated with VYALEV compared to 3% of patients who received placebo subcutaneous infusion. In Study 1, 5% of patients treated with VYALEV and 2% who received placebo withdrew from treatment because of an infusion site infection. The most frequent infusion site infection reported was cellulitis. If an infection is suspected at the infusion site, the cannula should be removed from the infusion site. If the cannula is removed for an infection, either a new canula should be placed at a new infusion site or, in the event of a prolonged interruption, the patient should be prescribed an oral carbidopa and levodopa product until they are able to resume VYALEV [see Dosage and Administration (2.3, 2.4)].

5.5 Withdrawal-Emergent Hyperpyrexia and Confusion

A symptom complex that resembles neuroleptic malignant syndrome (characterized by elevated temperature, muscular rigidity, altered consciousness, and autonomic instability), with no other obvious etiology, has been reported in association with rapid dose reduction, withdrawal of, or changes in dopaminergic therapy. Avoid sudden discontinuation or rapid dose reduction in patients taking VYALEV. If VYALEV is discontinued, the dose should be tapered to reduce the risk of hyperpyrexia and confusion [see Dosage and Administration (2.4)].

5.6 Dyskinesia

VYALEV may cause or exacerbate dyskinesias. In Study 1, dyskinesia occurred in 11% of patients treated with VYALEV compared to 6% of patients treated with oral immediate-release carbidopa-levodopa. The occurrence of dyskinesias may require a dosage reduction of VYALEV or other medications used to treat PD.

5.7 Cardiovascular Ischemic Events

In clinical studies, myocardial infarction and arrhythmia were reported in patients taking carbidopa-levodopa (the active metabolites of VYALEV). Ask patients about symptoms of ischemic heart disease and arrhythmia, especially those with a history of myocardial infarction or cardiac arrhythmias.

5.8 Glaucoma

Carbidopa-levodopa (the active metabolites of VYALEV) may cause increased intraocular pressure in patients with glaucoma. Monitor intraocular pressure in patients with glaucoma after starting VYALEV.

6 ADVERSE REACTIONS

The following serious adverse reactions are discussed below and elsewhere in labeling:

- Falling Asleep During Activities of Daily Living and Somnolence [see Warnings and Precautions (5.1)]
- Hallucinations/Psychosis [see Warnings and Precautions (5.2)]
- Impulse Control/Compulsive Behaviors [see Warnings and Precautions (5.3)]
- Infusion Site Reactions and Infections [see Warnings and Precautions (5.4)]
- Withdrawal-Emergent Hyperpyrexia and Confusion [see Warnings and Precautions (5.5)]
- Dyskinesia [see Warnings and Precautions (5.6)]
- Cardiovascular Ischemic Events [see Warnings and Precautions (5.7)]
- Glaucoma [see Warnings and Precautions (5.8)]

6.1 Clinical Trials Experience

Because clinical trials are conducted under widely varying conditions, adverse reaction rates observed in the clinical trials of a drug cannot be directly compared to rates in the clinical trials of another drug and may not reflect the rates observed in clinical practice.

In Study 1, a 12-week, active-controlled clinical trial, a total of 141 patients with advanced PD were enrolled [see Clinical Studies (14)]. Of these, 74 patients received VYALEV and 67 received oral immediate-release carbidopa-levodopa with placebo subcutaneous infusion.

Adverse reactions led to discontinuation of VYALEV in 22% of patients, which included hallucinations, infusion site reactions, and infusion site infections [see Warnings and Precautions (5.2, 5.5)]. Table 2 presents the adverse reactions that occurred in ≥3% of patients who received VYALEV and with a difference of >2% between the VYALEV and the oral immediate release carbidopa-levodopa groups in Study 1.

Table 2. Adverse Reactions in Study 1 that Occurred in ≥3% of Patients with Advanced PD who Received VYALEV and 2% Difference from Active Control
Adverse Reaction | VYALEV (n = 74) % | Oral immediate-release carbidopa-levodopa (n = 67) %
Infusion/catheter site reactiona | 62 | 8
Infusion/catheter site infectionb | 28 | 3
Hallucination | 12 | 2
Dyskinesia | 11 | 6
On and off phenomenon | 8 | 0
Balance disorder | 5 | 0
Constipation | 5 | 0
Peripheral swelling | 5 | 0
Agitation | 4 | 2
Insomnia | 4 | 2
Psychotic disorderc | 4 | 2
Dyspnea | 4 | 0
1. Infusion/catheter site reaction includes multiple related terms.
2. Infusion site/catheter site infections includes multiple related terms.
3. Psychotic disorder includes psychotic disorder, delusion, and paranoia.

7 DRUG INTERACTIONS

7.1 Monoamine Oxidase (MAO) Inhibitors

Nonselective MAO Inhibitors

The use of nonselective MAO inhibitors (e.g., phenelzine and tranylcypromine) with VYALEV is contraindicated [see Contraindications (4)]. Discontinue use of any nonselective MAO inhibitors at least two weeks prior to initiating VYALEV.

Selective MAO Inhibitors

The use of selective MAO-B inhibitors (e.g., rasagiline and selegiline) with VYALEV may be associated with orthostatic hypotension. Monitor patients who are taking these drugs.

7.2 Antihypertensive Drugs

The concurrent use of VYALEV with antihypertensive medications can cause symptomatic postural hypotension. A dose reduction of the antihypertensive medication may be needed after starting or increasing the dosage of VYALEV.

7.3 Dopamine D2 Receptor Antagonists and Isoniazid

Dopamine D2 receptor antagonists (e.g., phenothiazines, butyrophenones, risperidone, metoclopramide, papaverine) and isoniazid may reduce the effectiveness of foslevodopa. Monitor patients for worsening Parkinson’s symptoms when patients are taking these medications with VYALEV.

8 USE IN SPECIFIC POPULATIONS

8.1 Pregnancy

Risk Summary

There are no data on the developmental risk associated with the use of VYALEV (foscarbidopa and foslevodopa) in pregnant women. Foscarbidopa is a prodrug of carbidopa, and foslevodopa is a prodrug of levodopa. In animal studies, carbidopa-levodopa has been shown to be developmentally toxic (including teratogenic effects) at clinically relevant doses (see Data).

The estimated background risk of major birth defects and miscarriage in the indicated population is unknown. In the U.S. general population, the estimated background risk of major birth defects and miscarriage in clinically recognized pregnancies is 2% to 4% and 15% to 20%, respectively.

Data

Animal Data

When administered to pregnant rabbits throughout organogenesis, carbidopa-levodopa caused both visceral and skeletal malformations in fetuses at all doses and ratios of carbidopa-levodopa tested. No teratogenic effects were observed when carbidopa-levodopa was administered to pregnant mice throughout organogenesis. There was a decrease in the number of live pups delivered by rats receiving carbidopa-levodopa during organogenesis.

8.2 Lactation

Risk Summary

Foscarbidopa and Foslevodopa

There are no adequate data on the presence of foscarbidopa or foslevodopa in human milk, the effects of foscarbidopa or foslevodopa on milk production or on the breastfed infant.

Foscarbidopa is a prodrug of carbidopa, and foslevodopa is a prodrug of levodopa.

Carbidopa

There are no adequate data on the presence of carbidopa in human milk, the effects on the breastfed infant, or the effects on milk production. Carbidopa is excreted in rat milk.

Levodopa

Levodopa has been detected in human milk after administration of carbidopa-levodopa. Levodopa decreases secretion of prolactin in humans, which may inhibit lactation. There are no adequate data on the effects of levodopa on the breastfed infant.

The developmental and health benefits of breastfeeding should be considered along with the mother’s clinical need for VYALEV and any potential adverse effects on the breastfed infant from VYALEV or from the underlying maternal condition.

8.4 Pediatric Use

Safety and effectiveness in pediatric patients have not been established.

8.5 Geriatric Use

Clinical studies of VYALEV did not include sufficient numbers of subjects aged 65 and over to determine whether they respond differently from younger subjects. Other reported clinical experience has not identified differences in responses between the elderly and younger patients. In general, dose selection for an elderly patient should be cautious, usually starting at the low end of the dosing range, reflecting the greater frequency of decreased hepatic, renal, or cardiac function and of concomitant disease or other drug therapy.

10 OVERDOSAGE

In the event of an overdosage with VYALEV, the infusion should be stopped immediately. Administer intravenous fluids and maintain an adequate airway. Electrocardiographic monitoring should be used, and the patient observed carefully for the development of cardiac arrhythmias; if necessary, an appropriate antiarrhythmic therapy should be given. Patients must also be monitored for hypotension.

11 DESCRIPTION

VYALEV injection is a solution that is a combination of foscarbidopa (carbidopa-4´-monophosphate) and foslevodopa (levodopa-4´-monophosphate).

Foscarbidopa and foslevodopa are prodrugs that undergo enzymatic bioconversion via intrinsic alkaline phosphatase to carbidopa and levodopa, respectively, in vivo.

Foscarbidopa, an inhibitor of aromatic amino acid decarboxylation, is a white to light yellow powder, freely soluble in aqueous media, with a molecular weight of 306.21 g/mol anhydrous. It is designated chemically as (2S)-2-hydrazinyl-3-[3-hydroxy-4-(phosphonooxy)phenyl]-2-methylpropanoic acid trihydrate. Its empirical formula is C10H15N2O7P (anhydrous basis), and its structural formula is:

Foslevodopa, an aromatic amino acid, is a white to off-white powder, freely soluble in aqueous media, with a molecular weight of 277.17 g/mol. It is designated chemically as (2S)-2-amino-3-[3-hydroxy-4-(phosphonooxy)phenyl] propanoic acid. Its empirical formula is C9H12NO7P, and its structural formula is:

VYALEV (foscarbidopa and foslevodopa) injection is a sterile, preservative-free solution for subcutaneous infusion. VYALEV is supplied in a 10 mL single-dose glass vial that contains 120 mg foscarbidopa and 2,400 mg foslevodopa per 10 mL (12 mg foscarbidopa and 240 mg foslevodopa per mL). VYALEV may contain sodium hydroxide and/or hydrochloric acid to adjust the pH to approximately 7.4.

12 CLINICAL PHARMACOLOGY

12.1 Mechanism of Action

VYALEV is a prodrug combination of foscarbidopa (carbidopa-4´-monophosphate) and foslevodopa (levodopa-4´-monophosphate). Foscarbidopa and foslevodopa are converted in vivo to carbidopa and levodopa.

Carbidopa

When levodopa is administered orally, it is rapidly decarboxylated to dopamine in extracerebral tissues so that only a small portion of a given dose is transported unchanged to the central nervous system. Carbidopa inhibits the decarboxylation of peripheral levodopa, making more levodopa available for delivery to the brain.

Levodopa

Levodopa is the metabolic precursor of dopamine, does cross the blood-brain barrier, and presumably is converted to dopamine in the brain. This is thought to be the mechanism whereby levodopa treats symptoms of Parkinson's disease.

12.2 Pharmacodynamics

Because the decarboxylase inhibiting activity is limited to extracerebral tissues, administration of carbidopa with levodopa makes more levodopa available to the brain. The addition of carbidopa to levodopa reduces the peripheral effects (e.g., nausea and vomiting) due to decarboxylation of levodopa; however, carbidopa does not decrease the adverse reactions due to the central effects of levodopa.

12.3 Pharmacokinetics

Absorption

VYALEV is administered directly into the subcutaneous space and is converted to carbidopa and levodopa by alkaline phosphatase. In a phase 1 study in healthy volunteers, carbidopa and levodopa were detectable in plasma within 30 minutes at the first pharmacokinetic (PK) collection point. In healthy volunteer subjects the steady state levodopa was achieved within 2 hours when VYALEV dosing was delivered as a loading dose followed by continuous infusion.

Healthy volunteers were administered VYALEV to different subcutaneous sites (i.e., abdomen, arm, and thigh) using a 3-way crossover design. PK analysis from this study showed that the 3 sites provided comparable carbidopa and levodopa exposure suggesting VYALEV absorption is similar at the different subcutaneous sites.

Effect of Food

VYALEV bypasses the gut, so consumption of food does not change absorption or systemic exposure of carbidopa/levodopa.

Distribution

Both foslevodopa and foscarbidopa have binding to plasma proteins between 24% to 26%.

Levodopa

Levodopa is distributed between erythrocytes and plasma in approximately 1:1 ratio. Levodopa binding to plasma proteins is< 10%. Levodopa is transported into the brain by the carrier mechanism for large neutral amino acids.

Carbidopa

Carbidopa is approximately 36% bound to plasma protein. Carbidopa does not cross the blood-brain barrier.

Metabolism and Excretion

The foscarbidopa and foslevodopa from VYALEV are converted by alkaline phosphatases into carbidopa and levodopa.

Levodopa

Levodopa is mainly eliminated via metabolism by the aromatic amino acid decarboxylase (AAAD) and the catechol-O-methyl-transferase (COMT) enzymes. Other routes of metabolism are transamination and oxidation. The decarboxylation of levodopa to dopamine by AAAD is the major enzymatic pathway when no enzyme inhibitor is co-administered. O-methylation of levodopa by COMT forms 3-O-methyldopa. When administered with carbidopa, the elimination half-life of levodopa is approximately 1.5 hours.

Carbidopa

Carbidopa is metabolized to two main metabolites (α-methyl-3-methoxy-4-hydroxyphenylpropionic acid and α-methyl-3,4-dihydroxyphenylpropionic acid). These 2 metabolites are primarily eliminated in the urine unchanged or as glucuronide conjugates. Unchanged carbidopa accounts for 30% of the total urinary excretion. The elimination half-life of carbidopa is approximately 2 hours.

13 NONCLINICAL TOXICOLOGY

13.1 Carcinogenesis, Mutagenesis, Impairment of Fertility

Carcinogenesis

In rat, oral administration of carbidopa and levodopa for two years resulted in no evidence of carcinogenicity. VYALEV contains hydrazine, a degradation product of carbidopa. In published studies, hydrazine has been demonstrated to be carcinogenic in multiple animal species. Increases in liver (adenoma, carcinoma) and lung (adenoma, adenocarcinoma) tumors have been reported with oral administration of hydrazine in mouse, rat, and hamster.

Mutagenesis

Carbidopa was positive in the in vitro Ames test, in the presence and absence of metabolic activation, and the in vitro mouse lymphoma tk assay in the absence of metabolic activation but was negative in the in vivo mouse micronucleus assay.

In published studies, hydrazine was reported to be positive in in vitro genotoxicity (Ames, chromosomal aberration in mammalian cells, and mouse lymphoma tk) assays and in the in vivo mouse micronucleus assay.

Impairment of Fertility

In reproduction studies, no effects on fertility were observed in rats receiving carbidopa and levodopa.

14 CLINICAL STUDIES

The efficacy of VYALEV was established in a 12-week, randomized, double-blind, double-dummy, active-controlled, multicenter study (Study 1; NCT04380142) in patients with advanced Parkinson’s disease (PD). Study 1 enrolled patients who were responsive to levodopa treatment, had motor fluctuations inadequately controlled by their current medications, and who experienced a minimum of 2.5 hours of “Off” time per day as assessed by PD diaries. A total of 141 patients were randomized in 1:1 ratio and received either 24-hour/day continuous subcutaneous administration of VYALEV plus oral placebo capsules (N=74) or 24-hour/day continuous subcutaneous administration of placebo solution plus oral encapsulated carbidopa-levodopa immediate-release (IR) tablets (N=67).

Patients had a mean age of 66.4 years and a mean disease duration of 8.6 years. Most (93%) of the patients were white, 2% were Asian, 3% Black and 70% of the patients were male. At baseline, approximately 74% of patients in the VYALEV group and 66% of patients in the oral IR carbidopa-levodopa group were taking at least 1 or more classes of PD medications other than carbidopa-levodopa.

The primary clinical outcome measure was the mean change from baseline to Week 12 in the total daily mean “On” time without troublesome dyskinesia (defined as "On" time without dyskinesia plus "On" time with non-troublesome dyskinesia) based on PD diary.

The key secondary clinical outcome measure was the mean change from baseline to Week 12 in the total daily mean “Off” time. The “On” and “Off” time were normalized to a daily 16-hour awake period. Daily normalized "Off" and "On" times are averaged over valid PD diary days for each visit to obtain the average daily normalized times. VYALEV demonstrated statistically significant improvements from baseline to Week 12 in "On" time without troublesome dyskinesia compared with the oral IR carbidopa-levodopa group (p=0.0083; Table 3). VYALEV also demonstrated statistically significant improvements from baseline to Week 12 in “Off” time compared with the oral IR carbidopa-levodopa group (p=0.0054; Table 3).

Table 3. Change from Baseline to Week 12 in Primary and Key Secondary Measures
 | Oral IR carbidopa-levodopab (N=67) | VYALEV (N=73)
Primary Measure
“On” time without troublesome dyskinesia (hours) a
Baseline Mean (SD) | 9.49 (2.62) | 9.20 (2.42)
Change from Baseline to Endpoint Week 12 Mean (SD) | 0.85 (3.46) | 3.36 (3.62)
LS Mean (SE) of Change | 0.97 (0.50) | 2.72 (0.52)
LS Mean (SE) of Difference | 1.75 (0.65)
P value | 0.0083
Secondary Measure
“Off” time (hours) a
Baseline Mean (SD) | 5.91 (1.88) | 6.34 (2.27)
Change from Baseline to Endpoint Week 12 Mean (SD) | -0.93 (3.31) | -3.41 (3.76)
LS Mean (SE) of Change | -0.96 (0.49) | -2.75 (0.50)
LS Mean (SE) of Difference | -1.79 (0.63)
P value | 0.0054
LS = least squares; SD = standard deviation; SE = standard error.
a Derived from Parkinson’s Disease (PD) diary.
b Oral immediate release carbidopa-levodopa tablets.

Figure 1 shows results over time according to treatment for the efficacy variable (mean change from baseline to week 12 in the total daily mean normalized “On” time without troublesome dyskinesia based on PD diary).

Figure 1. LS Mean Change (±SE) from Baseline in “On” Time Without Troublesome Dyskinesia over 12 Weeks

* p ≤ 0.01. P value reflects comparison between treatment groups

CD = carbidopa; LD = levodopa; LS = least squares; SE = standard error

Note - Week 3 was an optional visit.

Figure 2 shows results over time according to treatment for the efficacy variable (mean change from baseline to week 12 in the total daily mean normalized “Off” time based on PD diary).

Figure 2. LS Mean Change (±SE) from Baseline in “Off” Time over 12 Weeks

* p ≤ 0.01. P value reflects comparison between treatment groups

CD = carbidopa; LD = levodopa; LS = least squares; SE = standard error

Note - Week 3 was an optional visit.

16 HOW SUPPLIED/STORAGE AND HANDLING

16.1 How Supplied

VYALEV injection contains 120 mg foscarbidopa and 2,400 mg foslevodopa per 10 mL (12 mg foscarbidopa and 240 mg foslevodopa per mL) and is a colorless to yellow to brown (may have a purple or red tint), and clear to slightly opalescent solution. Each single-dose glass vial is filled with approximately 10 mL of solution and is fitted with a grey rubber stopper, aluminum crimp cap, and turquoise plastic flip-off cap.

The rubber stopper on the vial does not contain natural rubber latex.

Carton of 7 VYALEV vials: NDC 0074-0501-01

The VYAFUSER pump used to administer VYALEV (foscarbidopa and foslevodopa) is provided separately.

16.2 Storage and Handling

- Keep the medication vials in the outer carton to protect the vials from breaking.
- Store VYALEV refrigerated at 2°C to 8°C (36°F to 46°F).
- VYALEV may be stored at room temperature up to a maximum of 30°C (86°F) for a single period of up to 28 days.
  - Once VYALEV has been stored at room temperature, do not return the product to the refrigerator.
  - If stored at room temperature, discard VYALEV if not used within 28 days.
- Do not freeze.
- Do not shake.

17 PATIENT COUNSELING INFORMATION

Advise the patient to read the FDA-approved patient labeling (Medication Guide and Instructions for Use).

Administration Information

Refer patients to the Instructions for Use for complete administration instructions. Inform patients of aseptic technique and of subcutaneous administration site selection and rotation [see Dosage and Administration (2.3)]. Instruct the patient to record the date when VYALEV is first removed from the refrigerator in the space provided on the carton [see Storage and Handling (16.2)].

Interruption of VYALEV Infusion

Inform patients that if they disconnect the pump for less than 1 hour (e.g., to shower or for a short medical procedure), a new infusion set (tubing and cannula) or rotation of the infusion site is not needed before resuming infusion, unless medically indicated. Instruct the patient to stop the pump and disconnect the tubing. The syringe can remain attached to the pump until the tubing is reconnected. Refer the patient to the Patient Instructions for Use for additional information.

Inform patients that if they have a prolonged interruption of therapy lasting more than 1 hour, a new infusion set (tubing and cannula) should be used, and rotation to a different infusion site is required before resuming infusion. In addition, if VYALEV is interrupted for more than 3 hours, advise patients to administer a loading dose with either VYALEV or oral immediate-release carbidopa and levodopa [see Dosage and Administration (2.2)]. Instruct patients to have oral carbidopa and levodopa available in case treatment with VYALEV is interrupted for 1 hour or longer.

Falling Asleep during Activities of Daily Living and Somnolence

Alert patients to the potential sedating effects caused by VYALEV, including somnolence and the possibility of falling asleep while engaged in activities of daily living. Because somnolence is a common adverse reaction with potentially serious consequences, patients should not drive a car, operate machinery, or engage in other potentially dangerous activities until they have gained sufficient experience with VYALEV to gauge whether it affects their mental and/or motor performance adversely. Advise patients that if increased somnolence or episodes of falling asleep during activities of daily living (e.g., conversations, eating, driving a motor vehicle, etc.) are experienced at any time during treatment, they should not drive or participate in potentially dangerous activities until they have contacted their healthcare professional.

Advise patients of possible additive effects when patients are taking other sedating medications, alcohol, or other central nervous system depressants (e.g., benzodiazepines, antipsychotics, antidepressants, etc.) in combination with VYALEV or when taking a concomitant medication that increases plasma levels of levodopa [see Warnings and Precautions (5.1)].

Hallucinations/Psychosis/Confusion

Inform patients that they may experience hallucinations (unreal visions, sounds, or sensations) and other symptoms of psychosis while taking VYALEV. Tell patients to report hallucinations, abnormal thinking, psychotic behavior, or confusion to their healthcare professional promptly should they develop [see Warnings and Precautions (5.2)].

Impulse Control/Compulsive Behaviors

Advise patients that they may experience impulse control and/or compulsive behaviors while taking VYALEV. Advise patients to inform their healthcare professional if they develop new or increased gambling urges, sexual urges, uncontrolled spending, binge or compulsive eating, or other urges while being treated with VYALEV [see Warnings and Precautions (5.3)].

Infusion Site Reactions and Infections

Advise patients to contact their healthcare professional if they notice signs of inflammation or infection at the infusion site, such as local spreading of redness, swelling, warmth, pain, discoloration when they apply pressure to the area, and/or fever. Tell patients to follow aseptic techniques while using VYALEV and to regularly change the infusion site (at least every third day), using a new infusion set. Advise patients to make sure the new infusion site is at least 1 inch (2.5 cm) from a site used in the last 12 days. Instruct patients to remove the cannula if an infection at the infusion site occurs and to contact their healthcare provider. Inform patients that they may need to change the infusion site more often than every third day if they notice any of the above-mentioned signs of infection [see Warnings and Precautions (5.4)].

Withdrawal-Emergent Hyperpyrexia and Confusion

Advise patients to contact their healthcare professional before stopping VYALEV. Tell patients to inform their healthcare professional if they develop withdrawal symptoms such as fever, confusion, or severe muscle stiffness [see Warnings and Precautions (5.5)].

Dyskinesia

Inform patients that VYALEV may cause or exacerbate pre-existing dyskinesias [see Warnings and Precautions (5.6)].

Pregnancy

Advise patients to notify their healthcare provider if they become pregnant during treatment or plan to become pregnant during treatment [see Use in Specific Populations (8.1)].

Lactation

Advise patients to notify their healthcare provider if they are breastfeeding or plan to breastfeed [see Use in Specific Populations (8.2)].

Manufactured for:
AbbVie Inc.
North Chicago, IL 60064 U.S.A
VYALEV and its design are trademarks of AbbVie AB.
VYAFUSER™ is a trademark of AbbVie AB.
©2024 AbbVie. All rights reserved.
20065514 10-2024

Medication Guide
VYALEVTM (vye-uh-lev)
(foscarbidopa and foslevodopa)
injection, for subcutaneous use

What is the most important information I should know about VYALEV?
VYALEV may cause serious side effects, including:

- Falling asleep during activities of daily living and somnolence
- Hallucinations/psychosis, or confusion
- Impulse control, compulsive behaviors
- Infusion site reactions and infections
- Cardiovascular ischemic events

Some of these problems may require discussion with your healthcare provider.
See “What are the possible side effects of VYALEV?” for more information about side effects.

What is VYALEV?
VYALEV is a prescription medicine used for treatment of advanced Parkinson’s disease in adults. VYALEV contains two medicines, foscarbidopa and foslevodopa.
It is not known if VYALEV is safe and effective in children.

Do not use VYALEV if you:

- take a medicine called a nonselective monoamine oxidase (MAO) inhibitor or have taken a nonselective MAO inhibitor within the last 14 days.

Ask your healthcare provider or pharmacist if you are not sure if you take an MAO inhibitor.

Before using VYALEV, tell your healthcare provider about all your medical conditions, including if you:

- feel sleepy or have fallen asleep suddenly during the day.
- have or have been seeing things that are not there, hearing sounds or feeling sensations that are not real (hallucinations)
- have or have had unusual urges such as problems with gambling, compulsive eating, compulsive shopping, and increased sex drive.
- have trouble controlling your muscles (dyskinesia).
- have eye problems that cause increased pressure in your eye (glaucoma).
- drink alcohol. Alcohol can increase the chance that VYALEV will make you feel sleepy or fall asleep when you should be awake.
- have or have had heart problems, an abnormal heart rate or have had a heart attack in the past.
- have or have had high blood pressure (hypertension).
- are pregnant or plan to become pregnant. It is not known if VYALEV can harm your unborn baby.
- are breastfeeding or plan to breastfeed. Talk to your healthcare provider about the best way to feed your baby if you take VYALEV.

Tell your healthcare provider about all the medicines you take, including prescription and over-the-counter medicines, vitamins, and herbal supplements.
Using VYALEV with certain other medicines may affect each other and cause serious side effects.
Especially tell your healthcare provider if you take:

- medicines used to treat high blood pressure (hypertension)
- medicines used to treat depression called nonselective monoamine oxidase (MAO) inhibitor or have taken one within the last 14 days
- dopamine D2 receptor antagonists (antipsychotics or metoclopramide), and isoniazid

Ask your healthcare provider or pharmacist for a list of these medicines if you are not sure.

How should I use VYALEV?

- See the detailed “Instructions for Use of VYALEV” that comes with VYALEV for information on how to prepare syringes of VYALEV for use in the pump, and how to properly throw away (dispose of) used syringes.
- See the detailed “Patient Instructions for Use of VYAFUSER Pump” that comes with your pump for complete instructions on how to use the delivery system.
- Use VYALEV exactly as your healthcare provider tells you to use it.
- Only use VYALEV by yourself after you have been shown the right way to use VYALEV. Ask your healthcare provider if you have any questions.
- Your prescribed dose of VYALEV will be programmed into your pump by a healthcare provider and should only be changed by your healthcare provider.
- Do not stop using VYALEV unless you are told to do so by your healthcare provider.
- Talk with your healthcare provider about what to do in case you are unable to use VYALEV infusion.
- Keep a supply of backup oral Parkinson’s disease medicines that contain levodopa and carbidopa with you at all times.
- VYALEV is given continuously over 24 hours under the skin by a pump.
- VYALEV can be stopped for brief periods of time, such as when taking a shower or short medical procedure. Make sure to change your infusion set (tubing and cannula) and rotate to a different infusion site if you stop the infusion for longer than 1 hour.
- If VYALEV has been stopped for less than 1 hour you will not need a new infusion set (tubing and cannula) and you will not need to rotate to a different infusion site.
- If your infusions have been stopped for longer than 3 hours, consider also giving yourself a loading dose to quickly get your symptoms back under control.
- Have oral carbidopa and levodopa available in case your treatment with VYALEV is stopped for 1 hour or longer.
- You may call 866-4-VYALEV (866-489-2538) for additional help or go to www.vyalev.com.

What should I avoid while using VYALEV?

- Do not drive, operate machinery, or do other activities until you know how VYALEV affects you. Sleepiness and falling asleep suddenly caused by VYALEV can happen as late as 1 year after you start your treatment.

What are the possible side effects of VYALEV?

- See “What is the most important information I should know about VYALEV?”

VYALEV can cause serious side effects including:

- Seeing things that are not there, hearing sounds or feeling sensations that are not real (hallucinations). This is a common and sometimes serious side effect. Hallucinations can happen in people who use VYALEV. Tell your healthcare provider if you have hallucinations.
- Unusual urges. Some people taking certain medicines to treat Parkinson’s disease, including VYALEV, have reported problems, such as gambling, compulsive eating, compulsive shopping, and increased sex drive.
  If you or your family members notice that you are having unusual urges or behaviors, talk to your healthcare provider.
- Infusion site reactions and infections. This is a common and sometimes serious side effect. Some people using VYALEV have had reactions and infections at the infusion site. Remove your cannula and call your healthcare provider if you have any of the following symptoms of an infection.

- local spreading of redness
- swelling
- change in color when pressing on the area

- pain
- warmth
- fever

- To prevent infection, clean your infusion site the way your healthcare provider has shown you (aseptic technique) and change your infusion site at least every 3 days using a new infusion site that is at least 1 inch from a site you used in the last 12 days.
- Withdrawal-emergent fever (hyperpyrexia) and confusion. Call your healthcare provider if you have any of the following symptoms after stopping VYALEV:

- fever
- confusion
- severe muscle stiffness

- Uncontrolled sudden movements (dyskinesia). This is a common and sometimes serious side effect. If you have new dyskinesia, or your dyskinesia gets worse, tell your healthcare provider. This may be a sign that your dose of VYALEV or other medicines to control your Parkinson’s disease may need to be adjusted.
- Heart attack or other heart problems. Tell your healthcare provider if you have had increased blood pressure, a fast or irregular heartbeat or chest pain.
- Worsening of the increased pressure in your eye (glaucoma). The pressure in your eyes should be checked after starting VYALEV.

Tell your healthcare provider or get medical care right away if you have any of the above symptoms. Your healthcare provider will tell you if you should stop treatment with VYALEV and if needed, tell you how to discontinue VYALEV.
Tell your healthcare provider if you have any side effect that bothers you or does not go away.
These are not all of the possible side effects of VYALEV. For more information, ask your healthcare provider or pharmacist.
Call your doctor for medical advice about side effects. You may report side effects to FDA at 1-800-FDA-1088.

How should I store VYALEV?

- Keep the vials in the outer carton to protect the vials from breaking.
- Store VYALEV in the refrigerator between 36°F to 46°F (2°C to 8°C).
- Record the date when VYALEV is first removed from the refrigerator in the space provided on the carton.
- VYALEV may be stored at room temperature up to a maximum of 86°F (30°C) for a single period of up to 28 days.
- After VYALEV has been stored at room temperature, do not return the medicine to the refrigerator.
- If stored at room temperature, throw away (dispose of) VYALEV if not used within 28 days.
- Do not freeze.
- Do not shake.
- If VYALEV is stored in the refrigerator, take one VYALEV vial out of the carton and out of the refrigerator 30 minutes before use. Use the VYALEV at room temperature or you may not get the right amount of the medicine.

Keep VYALEV and all medicines out of the reach of children.

General information about the safe and effective use of VYALEV
Medicines are sometimes prescribed for purposes other than those listed in a Medication Guide. Do not use VYALEV for a condition for which it was not prescribed. Do not give VYALEV to other people, even if they have the same symptoms that you have. It may harm them.
If you would like more information, talk with your healthcare provider. You can ask your healthcare provider or pharmacist for information about VYALEV that is written for healthcare professionals.

What are the ingredients in VYALEV?
Active ingredients: foscarbidopa and foslevodopa
Inactive ingredients: Sterile water for injection. Sodium hydroxide and hydrochloric acid may be used to adjust the pH to 7.4.
Manufactured for AbbVie Inc. North Chicago, IL 60064 U.S.A.
©2024 AbbVie. All rights reserved.
VYALEV and its design are trademarks of AbbVie AB.
For more information, call 1-866-4-VYALEV (1-866-489-2538) or go to www.VYALEV.com.

This Medication Guide has been approved by the U.S. Food and Drug Administration
20065515

10/2024

INSTRUCTIONS FOR USE

VYALEV™ [vye-uh-lev]

(foscarbidopa and foslevodopa)

injection, for subcutaneous use

Read this Instructions for Use before you start using VYALEV and each time you get a new refill. There may be new information. This information does not take the place of talking to your healthcare provider about your medical condition or your treatment. This Instructions for Use contains information on how to prepare VYALEV.

Before using VYALEV:

- Only use VYALEV by yourself after you have been shown the right way to use VYALEV and the delivery system (see the Patient Instructions for Use of VYAFUSER Pump).
- Call your healthcare provider or call (866) 4-VYALEV or (866) 489-2538 for help or go to www.VYALEV.com.

How should I store VYALEV?

- Keep the vials in the outer carton to protect the vials from breaking.
- Store VYALEV in the refrigerator between 36°F to 46°F (2°C to 8°C).
- Record the date when VYALEV is first removed from the refrigerator in the space provided on the carton.
- VYALEV may be stored at room temperature up to a maximum of 86°F (30°C) for a single period of up to 28 days.
- After VYALEV has been stored at room temperature, do not return the medicine to the refrigerator.
- If stored at room temperature, throw away (dispose of) VYALEV if not used within 28-days.
- Do not freeze.
- Do not shake.
- If VYALEV is stored in the refrigerator, take one VYALEV vial out of the carton and out of the refrigerator 30 minutes before use. Use the VYALEV at room temperature or you may not get the right amount of the medicine.

Keep VYALEV and all medicines out of the reach of children.

Important Information:

Solution

- The VYALEV solution color may have changes in color and does not affect how well the medicine works. It may be colorless, or may have different colors anywhere between light yellow and brown, possibly with purple or red tint. It also may become darker while in the syringe.
- If refrigerated before use, remove the solution vial from refrigerated storage and allow to sit at room temperature out of direct sunlight for 30 minutes.
- Do not add any other liquid (dilute) the VYALEV solution or fill the syringe with anything other than what your healthcare provider prescribed.
- Do not use VYALEV if the expiration date (EXP:) shown on the carton and vial has passed.

Disposable Parts (Vial Adapter and Syringe)

- A new vial adapter must be used with each new vial of VYALEV.
- Do not use the VYALEV solution if it has been in the syringe for more than 24 hours.

A. Transfer VYALEV from Solution Vial to Syringe

1. Make sure your work space is clean.

Note: This will help to avoid contamination.

2. Gather supplies, including (see Figure A):

- Solution vial

- Syringe (not included in VYALEV carton)

- Vial adapter (not included in VYALEV carton)

- Alcohol pads (not included in VYALEV carton)

Figure A

3. Check over the parts for expiration and for any packaging damage. This should include:

- Solution vial (see Figure B)
- Vial adapter
- Syringe

- Check if the solution is the VYALEV solution prescribed by your healthcare provider.
- Do not use the VYALEV solution, vial adapter, or syringe if it is expired.
- Do not use any parts if their sterile packaging has been damaged before use.

Note: The product packaging for the infusion set, vial adapter, and syringe show that they are sterile and how they were sterilized.

Figure B

4. Check over the contents of the VYALEV vial (see Figure C). Check the following:

- No cloudiness of the liquid.
- No particles seen in the liquid.

Figure C

- Do not use if the VYALEV solution is cloudy or contains flakes or particles.

Note: If refrigerated before use, remove the VYALEV solution vial from refrigerated storage and allow to sit at room temperature, out of direct sunlight, for 30 minutes.

- If refrigerated, do not warm VYALEV (in solution vial or syringe) in any way other than letting it warm at room temperature. For example, do not warm in a microwave or in hot water.

5. Wash your hands with soap and water and dry them (see Figure D).

Figure D

6. Prepare VYALEV solution vial.

a. Remove the vial cap (see Figure E).

Figure E

b. Wipe the top of the solution vial with an alcohol pad and allow to dry (see Figure F).

Note: This will help to avoid contamination.

Figure F

7. Attach the vial adapter to the solution vial.

Read your Vial Adapter Instructions for Use for detailed steps.

Vial Adapter

8. Prepare the syringe.

- To decrease the risk of infections, do not let the tip of any disposable parts come into contact with any unclean surfaces. If the tip of the vial adapter or syringe comes into contact with an unclean surface, throw (discard) it away and get a new one.

1. Get a new syringe and remove it from its packaging.
2. Push up on the rubber plunger to fully push out all air (see Figure G).

Figure G

9. While holding the vial adapter firmly, attach the syringe to the vial adapter by pushing and then screwing it into place (see Figure H).

- Do not overtighten.

Figure H

10. Hold the syringe pointing straight up (vertically) with the solution vial above the syringe (see Figure I).

Figure I

11. Withdraw all of the medicine from the vial into the syringe.

1. While holding the syringe firmly in one hand, pull down the plunger rod with the other hand to withdraw all of the medicine in the solution vial into the syringe to around the 12 mL mark, or until you see air at the tip of the syringe (see Figure J).

Note: It is important to hold the syringe pointing straight up.

Note: Always withdraw all of the medicine in the solution vial into the syringe.

Note: You will see air (head space) at the tip of the syringe.

Figure J

12. Check for air bubbles.

- If there are large air bubbles, they must be removed. Air may affect if you get the right amount of medicine (your dose).
- As seen in Figure K, small bubbles are okay and the air at the tip of the syringe (the head space) is expected.
- As seen in Figure L, larger air bubbles are not okay. While the air at the top of the syringe (the head space) is expected, the larger bubbles are not.

1. If you see large air bubbles, continue with Section B: Manually Remove Air Bubbles.
2. If you see small air bubbles or do not see any air bubbles, skip the next section and go to Section C: Remove (Purge) Air from Syringe.

Figure K

Figure L

B. Manually Remove Air Bubbles

13. Bring the bubbles together into a single air bubble.

a. Slowly and gently rotate the syringe and tilt it back and forth (see Figure M).

- Do not shake or tap the syringe to remove the air bubbles.

Figure M

Note: If there are still air bubbles, bring the bubbles together by gently rotating the syringe end over end (see Figure N).

b. When the large air bubbles are brought together into a single air bubble, continue with the next step.

Figure N

C. Remove (Purge) Air from Syringe

14. Push air out of the syringe.

1. With the solution vial still attached, point the syringe upward.
2. Slowly push the air out of the syringe and into the vial (see Figure O).
3. Continue pushing until all of the air is pushed out the syringe and into the solution vial and you can see that there is solution in the syringe tip.

Figure O

Note: Some resistance will be felt as the air is pushed back into the solution vial.

Note: If the syringe is tilted slightly and not pointing straight up, you may see a small air bubble in the corner (see Figure P). This is okay.

Figure P

15. Turn the syringe and solution vial upside down (invert) so that the solution vial is upright on the table (see Figure Q).

Figure Q

16. Disconnect the syringe from the vial adapter.

a. Hold the vial adapter firmly with one hand and the barrel of the syringe with the other.

b. Unscrew the syringe from the vial adapter (see Figure R).

Note: When disconnecting the syringe from the Vial, do not push the plunger or else the solution will leak.

c. Place the syringe on a clean surface, making sure the syringe tip does not contact an unclean surface.

- To decrease the risk of infections, do not let the tip of any disposable part come into contact with any unclean surfaces. If the tip of the vial adapter or syringe comes into contact with an unclean surface, throw it away (discard) and get a new one.

Figure R

17. Your syringe is now ready for use. Refer to your pump manual (Patient Instructions for Use of VYAFUSER Pump) for the next steps.

Patient Instructions for Use

of VYAFUSER Pump

D. Disposing of VYALEV

18. Used solution vials with the vial adapters still attached should be thrown away (disposed of) in accordance with local regulations or as directed by your healthcare provider.

This Instructions for Use for VYALEV (foscarbidopa and foslevodopa) is to be used with the VYAFUSER pump (see the Patient Instructions for Use of VYAFUSER Pump).

Manufactured for:
AbbVie Inc. North Chicago, IL 60064 U.S.A.
VYALEV and its design are trademarks of AbbVie AB.
VYAFUSER™ is a trademark of AbbVie AB.
©2024 AbbVie. All rights reserved.
This Instructions for Use has been approved by the U.S. Food and Drug Administration.
Approved: 10/2024
20065527

PRINCIPAL DISPLAY PANEL

NDC: 0074-0501-01

ATTENTION PHARMACIST:

Dispense the accompanying

Medication Guide to each patient.

VAYALEV™

foscarbidopa and

foslevodopa

Injection

120 mg and 2,400 mg per 10 mL

(12 mg and 240 mg per mL)

For subcutaneous use

7 x 10 mL single-dose vials

abbvie